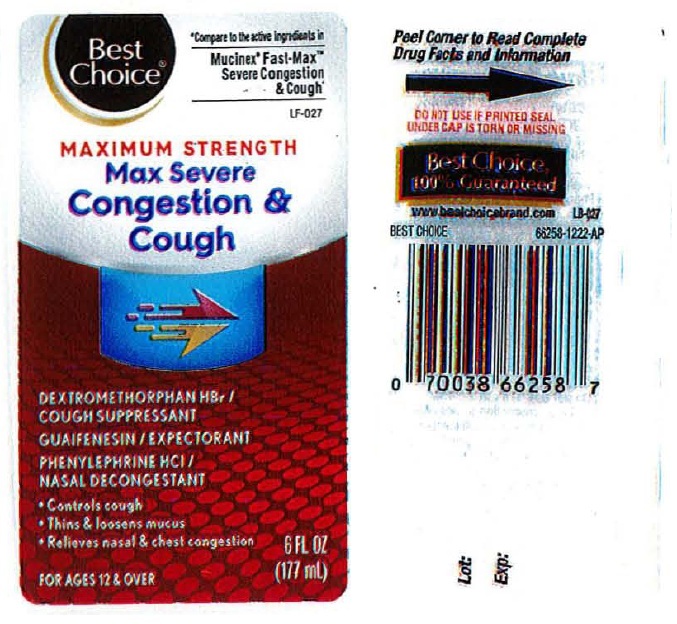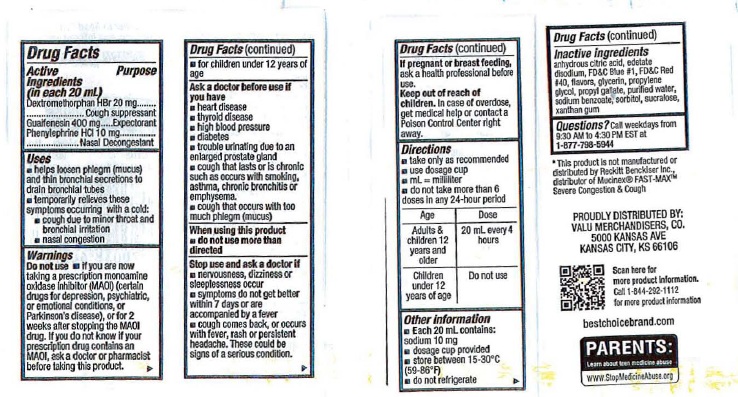 DRUG LABEL: Severe Congestion and Cough Max
NDC: 63941-517 | Form: SOLUTION
Manufacturer: Best Choice
Category: otc | Type: HUMAN OTC DRUG LABEL
Date: 20250128

ACTIVE INGREDIENTS: DEXTROMETHORPHAN HYDROBROMIDE 20 mg/20 mL; GUAIFENESIN 400 mg/20 mL; PHENYLEPHRINE HYDROCHLORIDE 10 mg/20 mL
INACTIVE INGREDIENTS: ANHYDROUS CITRIC ACID; EDETATE DISODIUM; FD&C BLUE NO. 1; FD&C RED NO. 40; GLYCERIN; PROPYLENE GLYCOL; PROPYL GALLATE; WATER; SODIUM BENZOATE; SORBITOL; SUCRALOSE; XANTHAN GUM

Best Choice Severe Congestion & Cough Max

Drug Facts

Active ingredients

(in each 20 mL)
Dextromethorphan HBr 20 mg
Guaifenesin 400 mg
Phenylephrine HCl 10 mg

Purpose

Dextromethorphan HBr ..........Cough suppressant
Guaifenesin ...........................Expectorant
Phenylephrine HCl ................. Nasal Decongestant

Uses

■ helps loosen pjlegm (mucus)
and thin bronchial secretions
to drain bronchial tubes
■ Temporarily relieves these symptoms ocurring with a cold:
■ cough due to minor throat and bronchial irritation
■ nasal congestion

Warnings

Do not use: ■ if you are now taking a prescription
monoamine oxidase inhibitor (MAOI) (certain
drugs for depression, psychiatric,
or emotional conditions, or Parkinson's
disease), or for 2 weeks after stopping the
MAOI drug. If you do not know if your
prescription drug contains an MAOI, ask
a doctor or pharmacist before taking this product.
■ for children under 12 years of age.

Ask a doctor before use if you have
■ heart disease
■ thyroid disease
■ high blood pressure
■ diabetes
■ trouble urinating due to an enlarged prostate gland
■ cough that lasts or is chronic
such as occurs with smoking, asthma,
chronic bronchitis or emphysema
■ cough that occurs with too much phlegm (mucus)

When using this product, do not use
more than directed

Stop use and ask a doctor if

■ nervousness, dizziness or sleeplessness occur
■ symptoms do not get better within 7 days or are accompanied by a fever
■ cough comes back, or occurs with fever, rash or persistent headache.

These could be signs of a serious condition.

PREGNANCY OR BREAST FEEDING

If pregnant or breast feeding ask a health professional before use.

Keep out of reach of children. In case of overdose, get
medical help or contact a Poison Control Center right
away.

Directions
■ take only as recommended
■ use dosage cup
■ mL= milliliter
■ do not take more than 6 doses in any 24-hour period

Age Dose
Adults & children 12 years and older | 20 mL every 4 hours
Children under 12 years of age | Do not use

Other information
■ Each 20 mL contains: sodium 10 mg
■ dosage cup provided
■ store between 15-30° C (59-86° F)
■ do not refrigerate

Inactive ingredients

anhydrous citric acid, edetate

disodium, FD&C Blue #1, FD&C Red

#40, flavors, glycerin, propylene

glycol, propyl gallate, purified water,

sodium benzoate, sorbitol, sucralose,

xanthan gum

QUESTIONS

Questions? Call weekdays from 9:30 AM to 4:30 PM EST at 1-877-798-5944

-----------

Product Label: Best Choice® Max Severe Congestion & Cough

Best Choice®

MAXIMUM STRENGTH

Max Severe Congestion & Cough

6 FL OZ (177 mL)

PROUDLY DISTRIBUTED BY:

VALUE MERCHANDISERS, CO.

5000 KANSAS AVE

KANSAS CITY, KS 66106

Compare to the active ingredients in

Mucinex® FAST-MAX™ Severe

Congestion & Cough*

*This product is not manufactured or

distributed by Reckitt Benckiser Inc.,

distributor of Mucinex® FAST-MAX™

Severe Congestion & Cough*

res